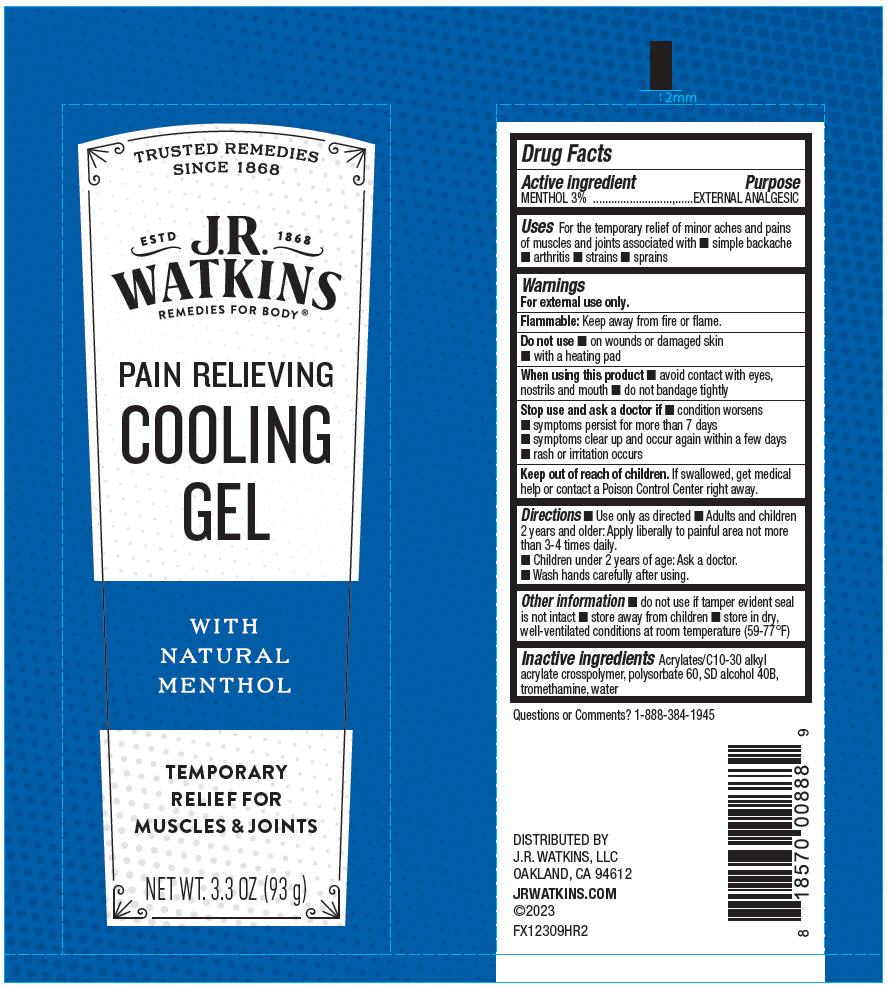 DRUG LABEL: Pain Relieving Cooling
NDC: 72342-020 | Form: GEL
Manufacturer: J.R. Watkins, LLC.
Category: otc | Type: HUMAN OTC DRUG LABEL
Date: 20240208

ACTIVE INGREDIENTS: MENTHOL, UNSPECIFIED FORM 3 g/100 g
INACTIVE INGREDIENTS: ALCOHOL; WATER; TROMETHAMINE; POLYSORBATE 60; CARBOMER INTERPOLYMER TYPE A (ALLYL SUCROSE CROSSLINKED)

Pain Relieving Cooling Gel

Drug Facts

Active Ingredient

MENTHOL 3%

Purpose

EXTERNAL ANALGESIC

Uses

For the temporary relief of minor aches and pains of muscles and joints associated with

- simple backache
- arthritis
- strains
- sprains

Warnings

For external use only.

Flammable:Keep away from fire or flame.

Do not use

- on wounds or damaged skin
- with a heading pad

When using this product

- avoid contact with eyes, nostrils and mouth
- do not bandage tightly

Stop use and ask a doctor if

- condition worsens
- symptoms persist for more than 7 days
- symptoms clear up and occur again within a few days
- rash or irritation occurs

Keep out of reach of children. If swallowed, get medical help or contact a Poison Control Center right away.

Directions

- Use only as directed
- Adults and children 2 years and older: Apply liberally to painful area not more than 3-4 times daily.
- Children under 2 years of age: Ask a doctor.
- Wash hands carefully after using

Other information

- do not use if tamper evident seal is not intact
- store away from children
- store in dry, well-ventilated conditions at room temperature (59-77°F)

Inactive ingredients

Acrylates/C10-30 alkyl acrylate crosspolymer, polysorbate 60, SD alcohol 40B, tromethamine, water

Questions or Comments?

1-888-384-1945

PRINCIPAL DISPLAY PANEL - 93 g Tube Label

TRUSTED REMEDIES
SINCE 1868

ESTD
1868

J.R.
WATKINS
REMEDIES FOR BODY®

PAIN RELIEVING
COOLING
GEL

WITH
NATURAL
MENTHOL

TEMPORARY
RELIEF FOR
MUSCLES & JOINTS

NET WT. 3.3 OZ (93 g)